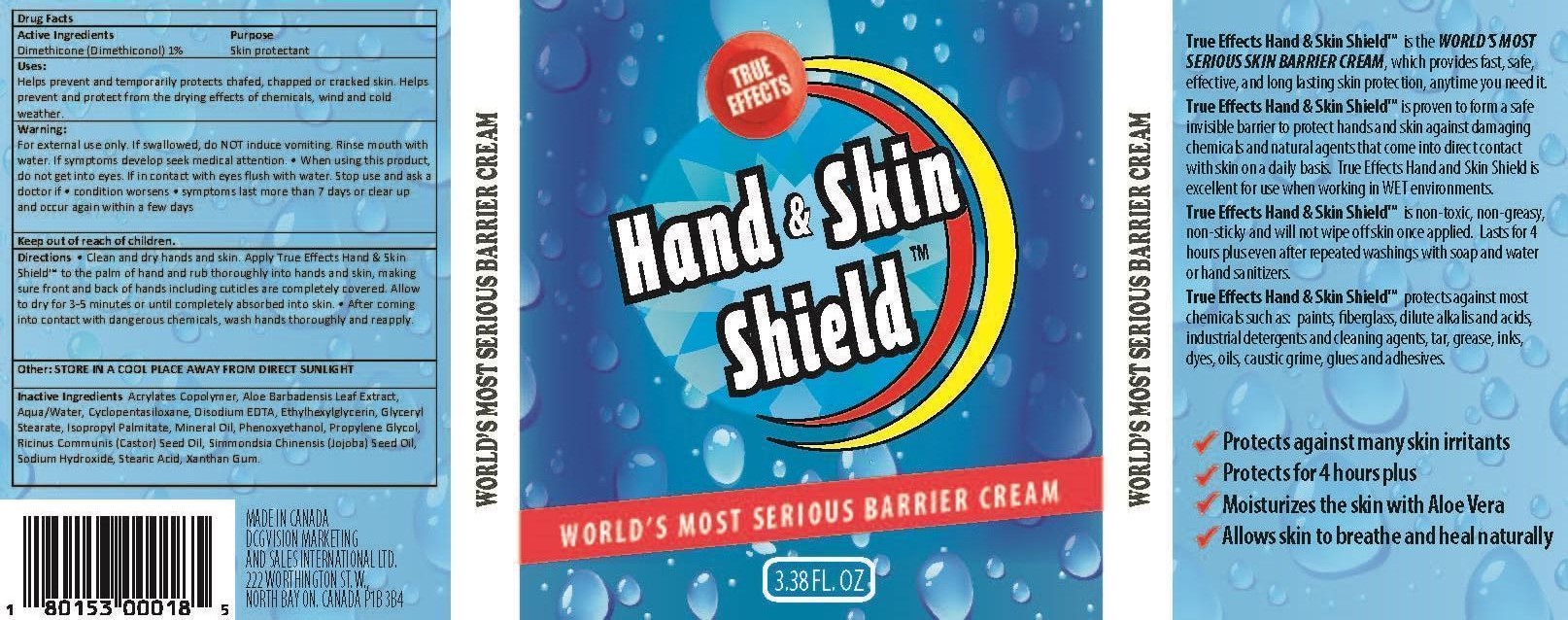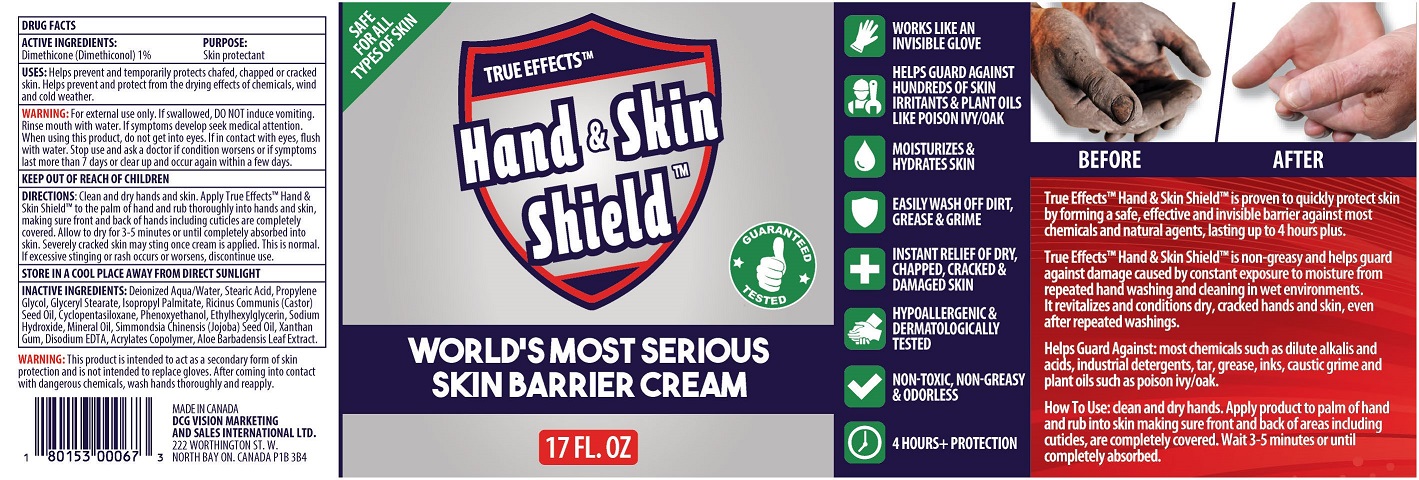 DRUG LABEL: HAND AND SKIN SHIELD
NDC: 69570-102 | Form: GEL
Manufacturer: DCG Vision Marketing & Sales International Ltd.
Category: otc | Type: HUMAN OTC DRUG LABEL
Date: 20211118

ACTIVE INGREDIENTS: DIMETHICONE 1 g/100 mL; MINERAL OIL 0.2 g/100 mL
INACTIVE INGREDIENTS: ETHYLHEXYLGLYCERIN; XANTHAN GUM; EDETATE DISODIUM; JOJOBA OIL; POLYACRYLIC ACID (8000 MW); ALOE VERA LEAF; STEARIC ACID; PROPYLENE GLYCOL; GLYCERYL MONOSTEARATE; ISOPROPYL PALMITATE; CASTOR OIL; CYCLOMETHICONE 5; PHENOXYETHANOL; SODIUM HYDROXIDE

DCG - HAND AND SKIN SHIELD (69570-102)

ACTIVE INGREDIENT(S)

MINERAL OIL 50%

PURPOSE

SKIN PROTECTANT

USES

Helps prevent and temporarily protects chafed, chapped or cracked skin. Helps prevent and protect from the drying effects of chemicals, wind and cold weather.

Keep out of reach of children.

WARNINGS

For external use only. If swallowed, do NOT induce vomiting. Rinse mouth with water. If symptoms develop seek medical attention. • When using this product, do not get into eyes. If in contact with eyes flush with water. Stop use and ask a doctor if • condition worsens • symptoms last more than 7 days or clear up and occur again within a few days

DIRECTIONS

• Clean and dry hands and skin. Apply True Effects Hand & Skin Shield™ to the palm of hand and rub thoroughly into hands and skin, making sure front and back of hands including cuticles are completely covered. Allow to dry for 3-5 minutes or until completely absorbed into skin. • After coming into contact with dangerous chemicals, wash hands thoroughly and reapply.

Other:

STORE IN A COOL PLACE AWAY FROM DIRECT SUNLIGHT

Inactive Ingredients:

Aqua/Water, Stearic Acid, Propylene Glycol, Glyceryl Stearate, Isopropyl Palmitate, Ricinus Communis (Castor) Seed Oil, Cyclopentasiloxane, Phenoxyethanol, Sodium Hydroxide, Dimethiconol, Ethylhexylglycerin, Xanthan Gum, Disodium EDTA, Simmondsia Chinensis (Jojoba) Seed Oil, Acrylates Copolymer, Aloe Barbadensis Leaf Extract.